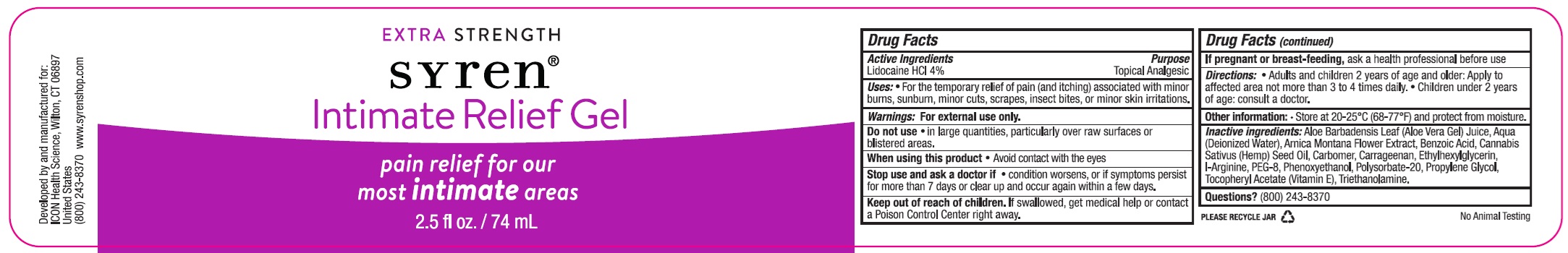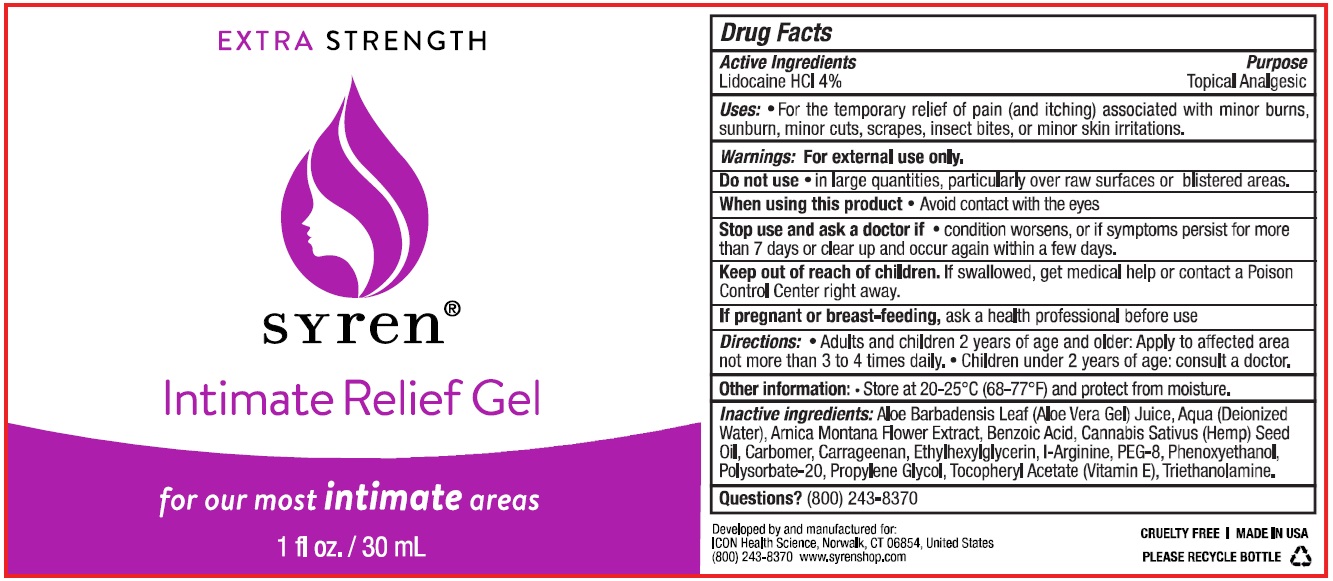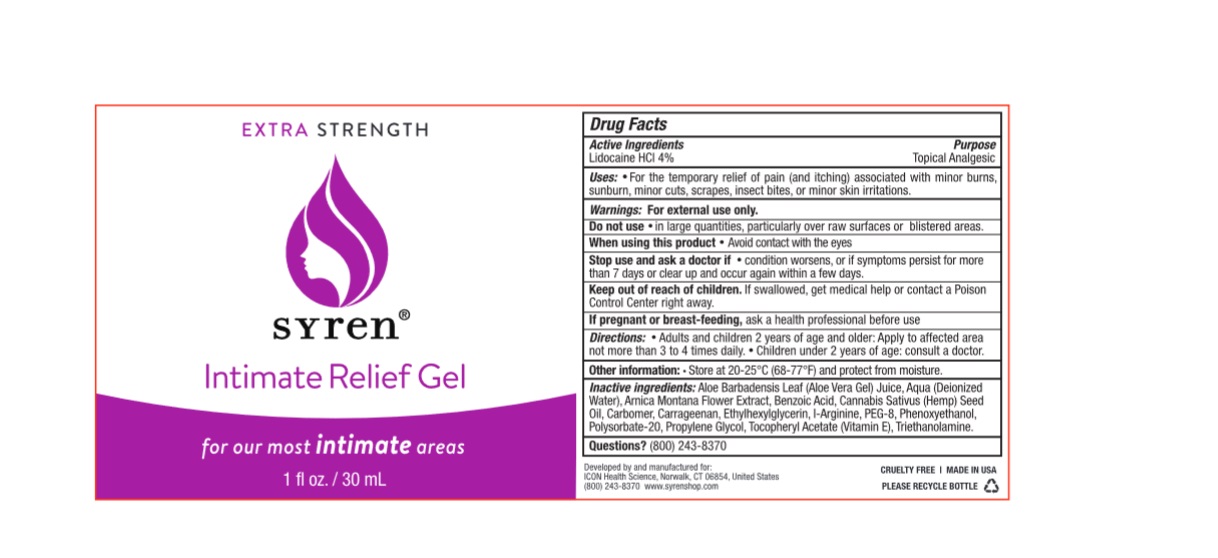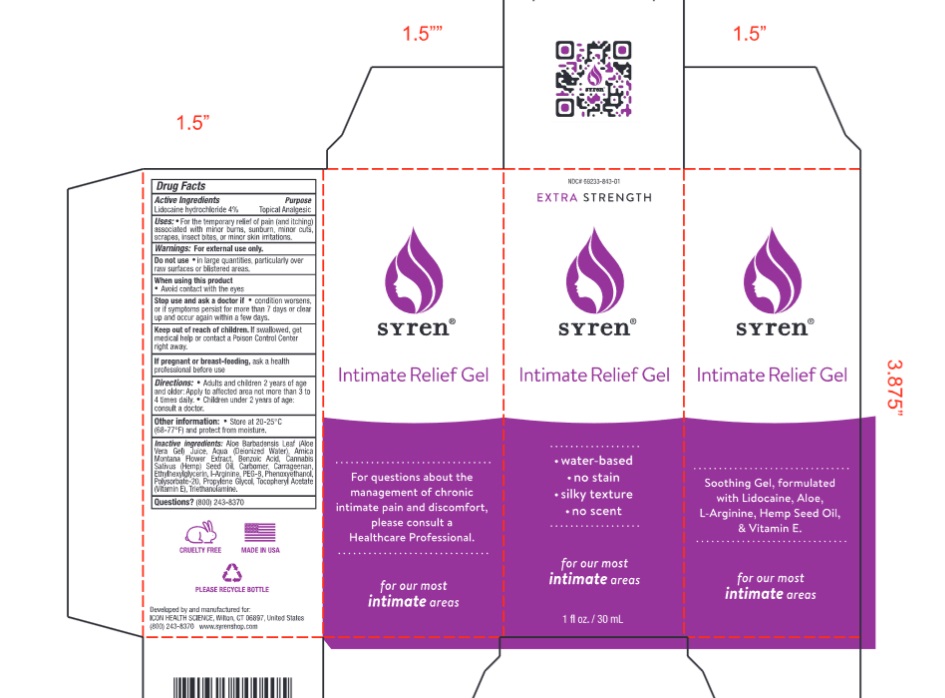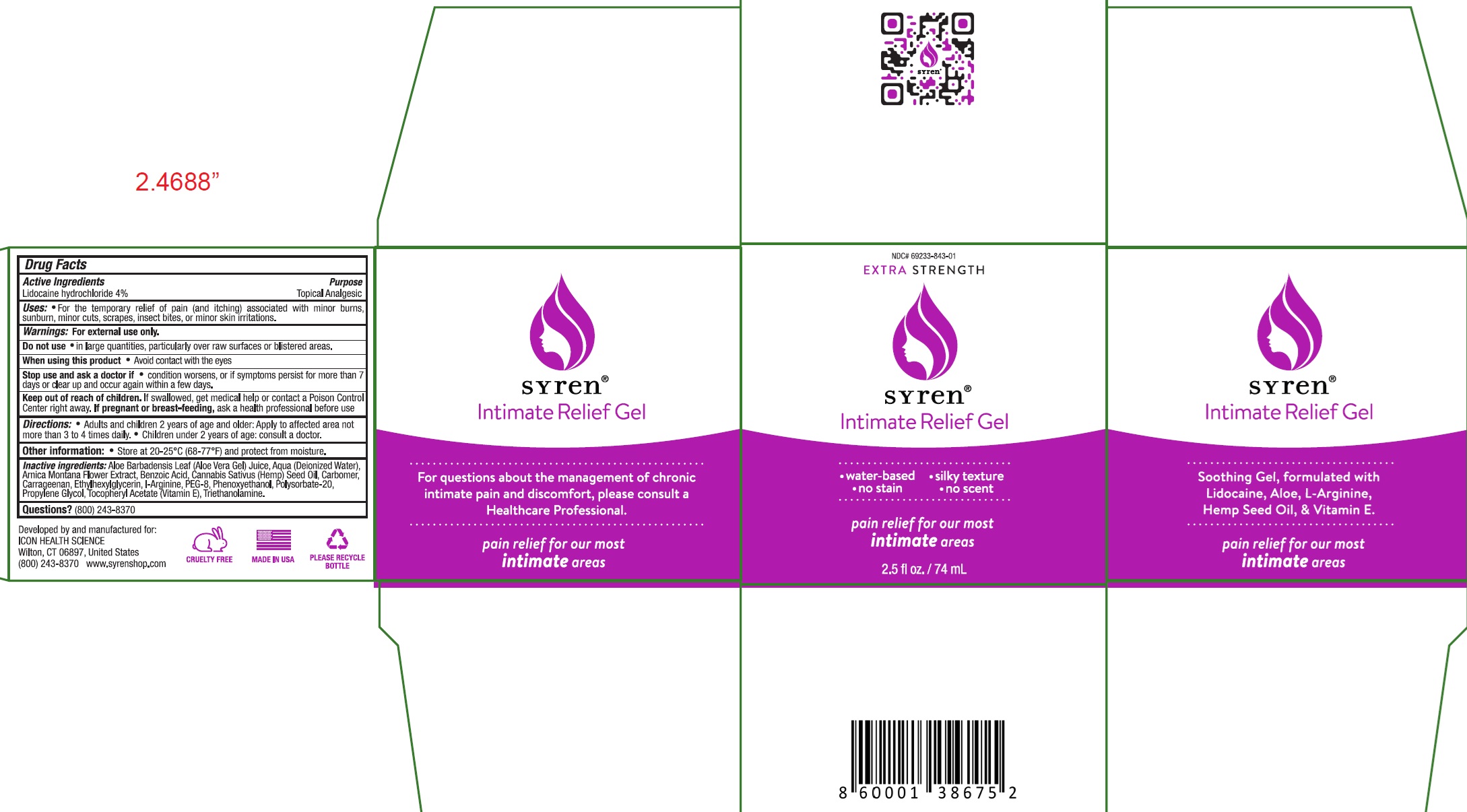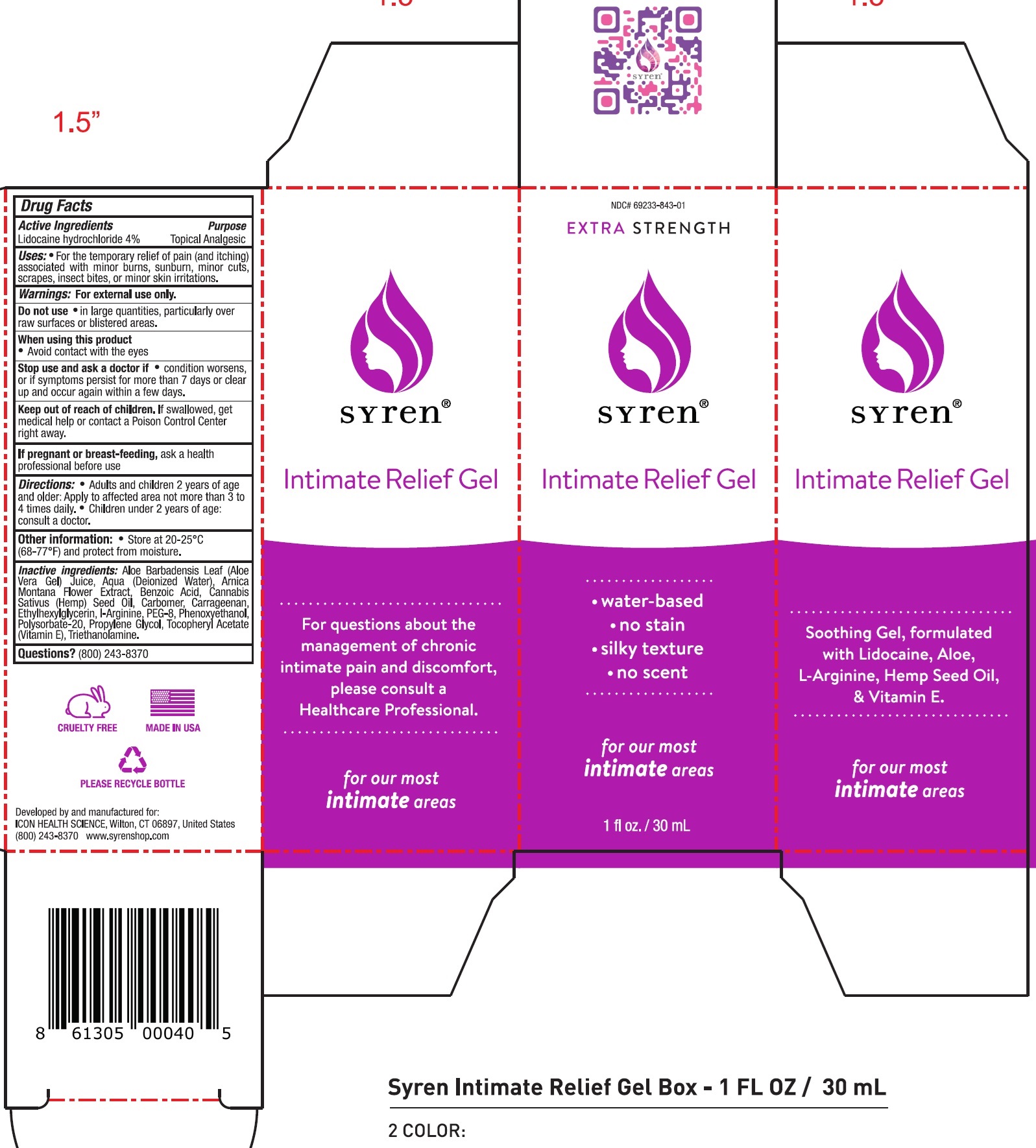 DRUG LABEL: SYREN Intimate Relief
NDC: 69233-843 | Form: GEL
Manufacturer: Icon Health Science
Category: otc | Type: HUMAN OTC DRUG LABEL
Date: 20240925

ACTIVE INGREDIENTS: LIDOCAINE HYDROCHLORIDE 40 mg/1 mL
INACTIVE INGREDIENTS: ALOE VERA LEAF; WATER; ARNICA MONTANA FLOWER; BENZOIC ACID; CANNABIS SATIVA SEED OIL; CARRAGEENAN; ETHYLHEXYLGLYCERIN; PHENOXYETHANOL; POLYSORBATE 20; PROPYLENE GLYCOL; .ALPHA.-TOCOPHEROL ACETATE; TROLAMINE

SYREN Intimate Relief Gel

Active Ingredient:

Lidocaine HCl 4.00%

PURPOSE

Topical Analgesic

Indications:

For the temporary relief of pain and itching, cuts, scrapes, and minor skin irritations.

Warnings:

- For external use only.
- Avoid contact with eyes.
- If symptoms persist for more than seven days discontinue use.

Keep out of reach of children.

If swallowed, consult physician.

- Do not apply to wounds or damaged skin.
- Wash hands after use.

PREGNANCY OR BREAST FEEDING

If pregnant or breast feeding, contact physician prior to use.

Directions:

- Adults and children two-years of age or older: Apply to affected area not more than three to four times daily.
- Children under twelve-years of age: consult a physician.

Additional Information:

Store at room temperature.

Other Ingredients:

Aloe Barbadensis Leaf (Aloe Vera Gel) Juice, Aqua (Deionized Water), Arnica Montana Flower Extract, Benzoic Acid, Cannabis Sativus (Hemp) Seed Oil, Carbomer, Carrageenan, Ethylhexylglycerin, I-Arginine, PEG-8, Phenoxyethanol, Polysorbate-20, Propylene Glycol, Tocopherol Acetate (Vitamin E), Triethanolamine.